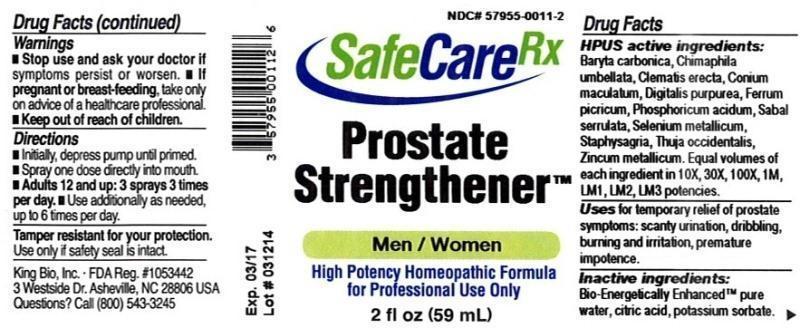 DRUG LABEL: Prostate Strengthener
NDC: 57955-0011 | Form: LIQUID
Manufacturer: King Bio Inc.
Category: homeopathic | Type: HUMAN OTC DRUG LABEL
Date: 20140331

ACTIVE INGREDIENTS: BARIUM CARBONATE 10 [hp_X]/59 mL; CHIMAPHILA UMBELLATA 10 [hp_X]/59 mL; CLEMATIS RECTA FLOWERING TOP 10 [hp_X]/59 mL; CONIUM MACULATUM FLOWERING TOP 10 [hp_X]/59 mL; DIGITALIS 10 [hp_X]/59 mL; PHOSPHORIC ACID 10 [hp_X]/59 mL; SAW PALMETTO 10 [hp_X]/59 mL; SELENIUM 10 [hp_X]/59 mL; DELPHINIUM STAPHISAGRIA SEED 10 [hp_X]/59 mL; THUJA OCCIDENTALIS LEAFY TWIG 10 [hp_X]/59 mL; ZINC 10 [hp_X]/59 mL
INACTIVE INGREDIENTS: WATER; CITRIC ACID MONOHYDRATE; POTASSIUM SORBATE

Prostate Strengthener

ACTIVE INGREDIENT

HPUS active ingredients: Baryta carbonica, Chimaphila umbellata, Clematis erecta, Conium maculatum, Digitalis purpurea, Phosphoricum acidum, Sabal serrulata, Selenium metallicum, Staphysagria, Thuja occidentalis, Zincum metallicum. Equal volumes of each ingredient in 10X, 30X, 100X, 1M, LM1, LM2, LM3 potencies.

PURPOSE

Uses for temporary relief of prostate symptoms: scanty urination, dribbling, burning and irritation, premature impotence.

Inactive Ingredients

Bio-Energetically Enhanced™ pure water base, Citric acid and Potassium sorbate.

Warning

- Stop use and ask a doctor. If symptoms persist or worsen.
- If pregnant or breast-feeding, take only on advice of a healthcare professional.

- Keep out of reach of children.

Directions

- Initially, depress pump until primed.
- Spray one dose directly into mouth.
- Adults 12 and up: 3 sprays 3 times per day.
- Use additonally as needed, up to 6 times per day.

Other Information: Tamper resistant for your protection. Use only if safety seal is intact.

INDICATIONS AND USAGE

Uses for temporary relief of prostate symptoms:

- scanty urination
- dribbling
- burning and irritation
- premature impotence